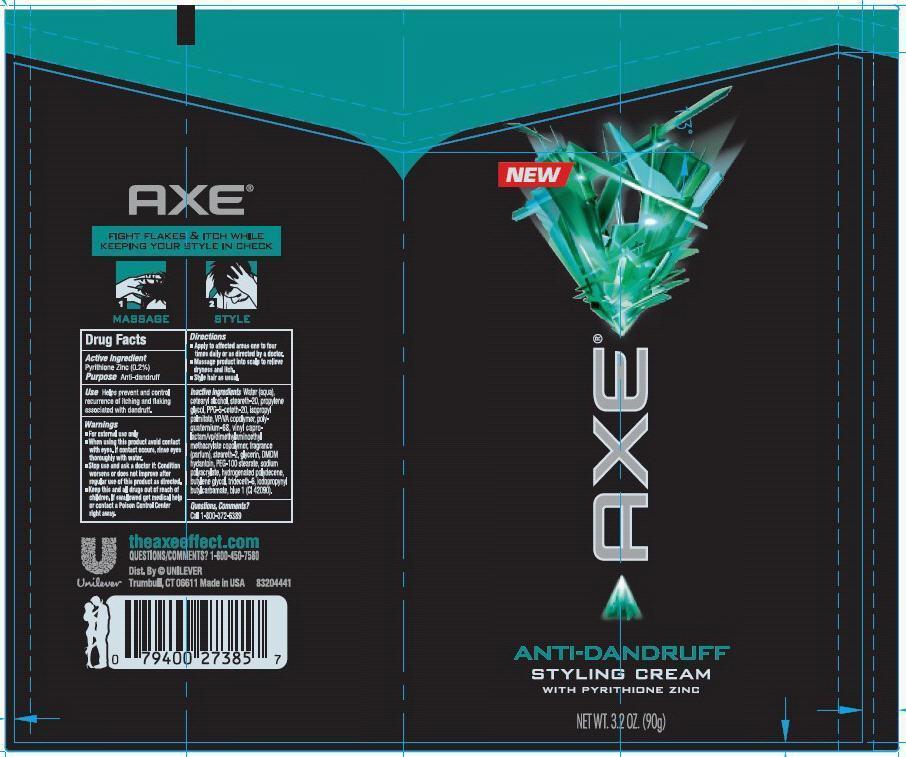 DRUG LABEL: Axe
NDC: 64942-1289 | Form: CREAM
Manufacturer: Conopco Inc. d/b/a Unilever
Category: otc | Type: HUMAN OTC DRUG LABEL
Date: 20130220

ACTIVE INGREDIENTS: Pyrithione Zinc 0.2 g/100 g
INACTIVE INGREDIENTS: WATER; CETOSTEARYL ALCOHOL; STEARETH-20; PROPYLENE GLYCOL; PPG-5-CETETH-20; ISOPROPYL PALMITATE; COPOVIDONE K25-31; STEARETH-2; GLYCERIN; DMDM HYDANTOIN; PEG-100 STEARATE; BUTYLENE GLYCOL; TRIDECETH-6; IODOPROPYNYL BUTYLCARBAMATE; FD&C BLUE NO. 1

Axe AntiDandruff Styling Cream

Active Ingredient

Pyrithione Zinc (0.2%)

Purpose

Anti-dandruff

Use

Helps prevent and control recurrence of itching and flaking associated with dandruff.

Warnings

• For external use only

• When using this product avoid contact with eyes. If contact occurs, rinse eyes thoroughly with water.

• Stop use and ask a doctor if: Condition worsens or does not improve after regular use of this product as directed.

KEEP OUT OF REACH OF CHILDREN

• Keep this and all drugs out of reach of children. If swallowed get medical help or contact a Poison Control Center right away.

Directions

• Apply to affected areas one to four times daily or as directed by a doctor.

• Massage product into scalp to relieve dryness and itch.

• Style hair as usual.

Inactive Ingredients:

Water (Aqua), Cetearyl Alcohol, Steareth-20, Propylene Glycol, PPG-5-Ceteth-20, Isopropyl Palmitate, VP/VA Copolymer, Polyquaternium-68, Vinyl Caprolactam/VP/Dimethylaminoethyl Methacrylate Copolymer, Fragrance (Parfum), Steareth-2, Glycerin, DMDM Hydantoin, PEG-100 Stearate, Sodium Polyacrylate, Hydrogenated Polydecene, Butylene Glycol, Trideceth-6, Iodopropynyl Butylcarbamate, Blue 1 (CI 42090)

Questions, Comments?

Call 1-800-372-6389